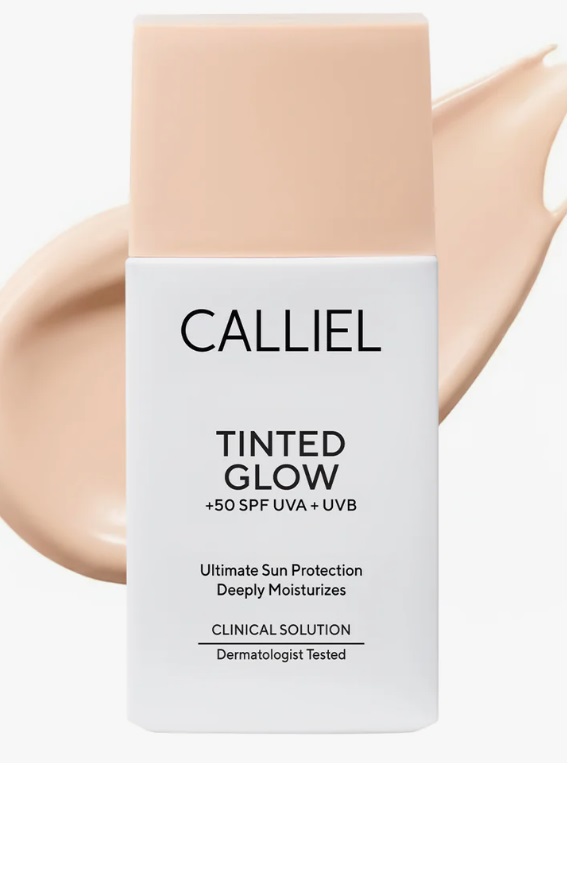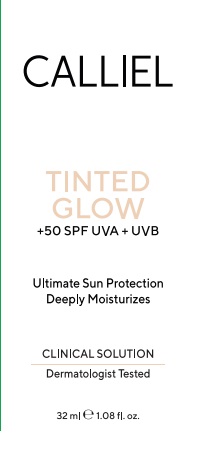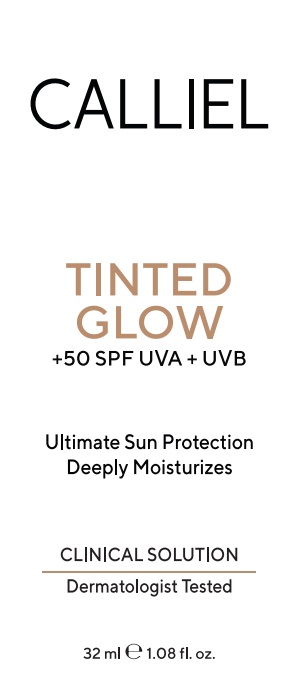 DRUG LABEL: CALLIEL Tinted Glow SPF 50 Medium
NDC: 87411-0002 | Form: CREAM
Manufacturer: CALLIEL PHARMA KOZMETIK SANAYI VE TICARET ANONIM SIRKETI
Category: otc | Type: HUMAN OTC DRUG LABEL
Date: 20260206

ACTIVE INGREDIENTS: TITANIUM DIOXIDE 3.5 g/100 g; AVOBENZONE 3.5 g/100 g; ZINC OXIDE 7 g/100 g; OCTINOXATE 7 g/100 g
INACTIVE INGREDIENTS: 2-ETHYLHEXYL ACRYLATE, METHACRYLATE, METHYL METHACRYLATE, OR BUTYL METHACRYLATE/HYDROXYPROPYL DIMETHICONE COPOLYMER (30000-300000 MW) 1 g/100 g; CAPRYLIC/CAPRIC TRIGLYCERIDE 6 g/100 g; CI 77492 0.6 g/100 g; GLYCERIN 3 g/100 g; ISOPROPYL MYRISTATE 2 g/100 g; CI 77499 0.3 g/100 g; PROPYLENE GLYCOL 2 g/100 g; BIS-PEG-10 DIMETHICONE/DIMER DILINOLEATE COPOLYMER 0.8 g/100 g; XYLITYLGLUCOSIDE 0.5 g/100 g; ANHYDROXYLITOL 0.3 g/100 g; BUTYROSPERMUM PARKII (SHEA) BUTTER 4 g/100 g; DIMETHICONE 3 g/100 g; C12-15 ALKYL BENZOATE 5 g/100 g; XYLITOL 0.3 g/100 g; DISTEARDIMONIUM HECTORITE 0.4 g/100 g; CI 77491 0.4 g/100 g; WATER 45.18 g/100 g; PHENOXYETHANOL 0.8 g/100 g; ALOE BARBADENSIS LEAF JUICE 0.1 g/100 g; TRIETHOXYCAPRYLYLSILANE 0.2 g/100 g; CAPRYLYL GLYCOL 0.12 g/100 g; CYCLOPENTASILOXANE 3 g/100 g

Active ingredients

Zinc Oxide 7%
Titanium Dioxide 3.5%
Avobenzone 3.5%
Octinoxate 7%

Uses

• helps prevent sunburn
• if used as directed with other sun protection measures (see Directions), decreases the risk of skin cancer and early skin aging caused by the sun

Do not use on damaged or broken skin

Stop use and ask a doctor if rash occurs.

Keep out of reach of children. If swallowed, get medical help or contact a Poison Control Center right away.

Directions

• apply liberally 15 minutes before sun exposure
• reapply:
• after 80 minutes of swimming or sweating
• immediately after towel drying
• at least every 2 hours
• children under 6 months: Ask a doctor

Sun Protection Measures: Spending time in the sun increases your risk of skin cancer and early skin aging caused by the sun. To decrease this risk, regularly use a sunscreen with a Broad Spectrum SPF 15 or higher and other sun protection measures including:
• limit time in the sun, especially from 10 a.m. – 2 p.m.
• wear long-sleeve shirts, pants, hats, and sunglasses

Warnings

For external use only

Purpose

Sunscreen

Inactive ingredients

Water, Caprylic/Capric Triglyceride, Butyrospermum Parkii Butter, C12-15 Alkyl Benzoate, Dimethicone, Glycerin, Propylene Glycol, Isopropyl Myristate, Cyclopentasiloxane, Acrylates/Dimethicone Copolymer, Xylitylglucoside, Phenoxyethanol, PEG-10 Dimethicone, Iron Oxides, Disteardimonium Hectorite, Anhydroxylitol, Xylitol, Aloe Barbadensis Leaf Extract, Caprylyl Glycol, Triethoxycaprylylsilane